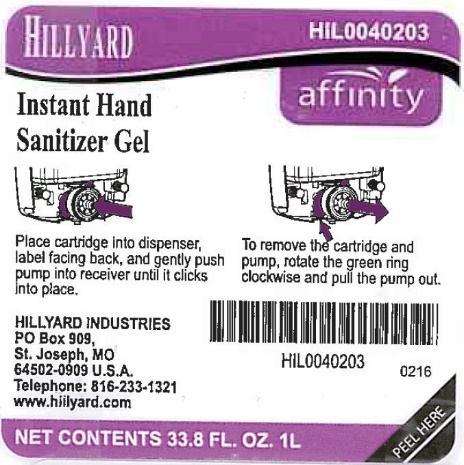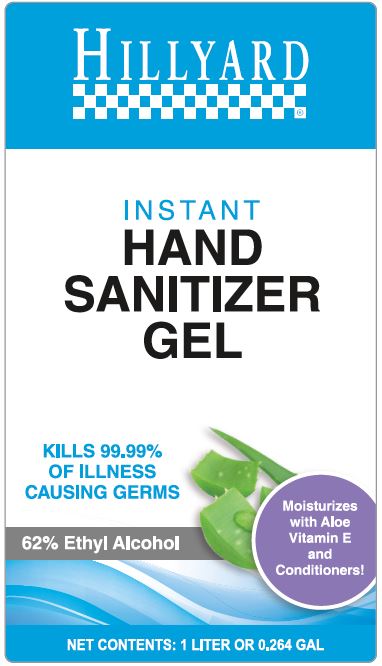 DRUG LABEL: Hillyard Instant Hand Sanitizer
NDC: 76402-402 | Form: GEL
Manufacturer: Hillyard GMP
Category: otc | Type: HUMAN OTC DRUG LABEL
Date: 20240118

ACTIVE INGREDIENTS: ALCOHOL 62 mL/100 mL
INACTIVE INGREDIENTS: WATER; CARBOMER INTERPOLYMER TYPE A (ALLYL SUCROSE CROSSLINKED); EDETOL; GLYCERIN; ANHYDROUS CITRIC ACID; .ALPHA.-TOCOPHEROL, D-; ALOE VERA LEAF

Hillyard Instant Hand Sanitizer Gel

Active Ingredients

Ethyl Alcohol 62.0%

Purpose

Antimicrobial

Uses

- For hand sanitizing to decrease bacteria on the skin
- Recommended for repeated use.

Warnings

For External Use Only.

Flammable. Keep away from fire or flame.

When using this product

avoid contact with eyes. In case of eye contact, flush eyes thoroughly with water.

Stop use and ask a doctor if

irritation or redness develops, or if condition persists for more than 72 hours.

Keep out of reach of children.

If swallowed, get medical help or contact a Poison Control Center right away.

Directions

- Pump small amount into palm of hand.
- Rub thoroughly over all surfaces of both hands.
- Rub hands together briskly until dry.
- Children under 6 years of age should be supervised when using this product.

Inactive Ingredients

Water, Acrylates/C10-C30 Alkyl Acrylate Crosspolymer, Tetrahydroxypropyl Ethylenediamine, Glycerine, Fragrance, Citric Acid, Vitamin E, Aloe Barbadensis Leaf Juice.

Package/Label Principal Display Panel

Hillyard
Instant Hand
Sanitizer Gel

HIL0040203

affinity

Place cartridge into dispenser, label facing back, and gently push pump into receiver until it clicks into place.

To remove the cartridge and pump, rotate the green ring clockwise and pull the pump out.

HILLYARD INDUSTRIES
PO Box 909,
St. Joseph, MO
64502-0909 U.S.A.
Telephone: 816-233-1321
www.hillyard.com

NET CONTENTS 33.8 FL. OZ. 1L

HIL0040203
0216
PEEL HERE

Label

Principal Display Panel – 1.00 Liter (Manual Dispensing Pump)

Hillyard

INSTANT HAND SANITIZER GEL

KILLS 99.99% OF ILLNESS CAUSING GERMS

Moisturizes with Aloe Vitamin E and Conditioners!

62% Ethyl Alcohol

NET CONTENTS: 1 LITER OR 0.264 GAL

HILLYARD INDUSTRIES, INC.
PO Box 909
St. Joseph, MO
64502-0909
Telephone: 800-365-1555
www.hillyard.com

Label